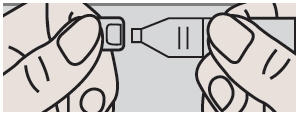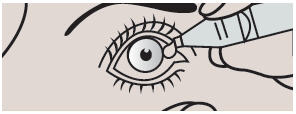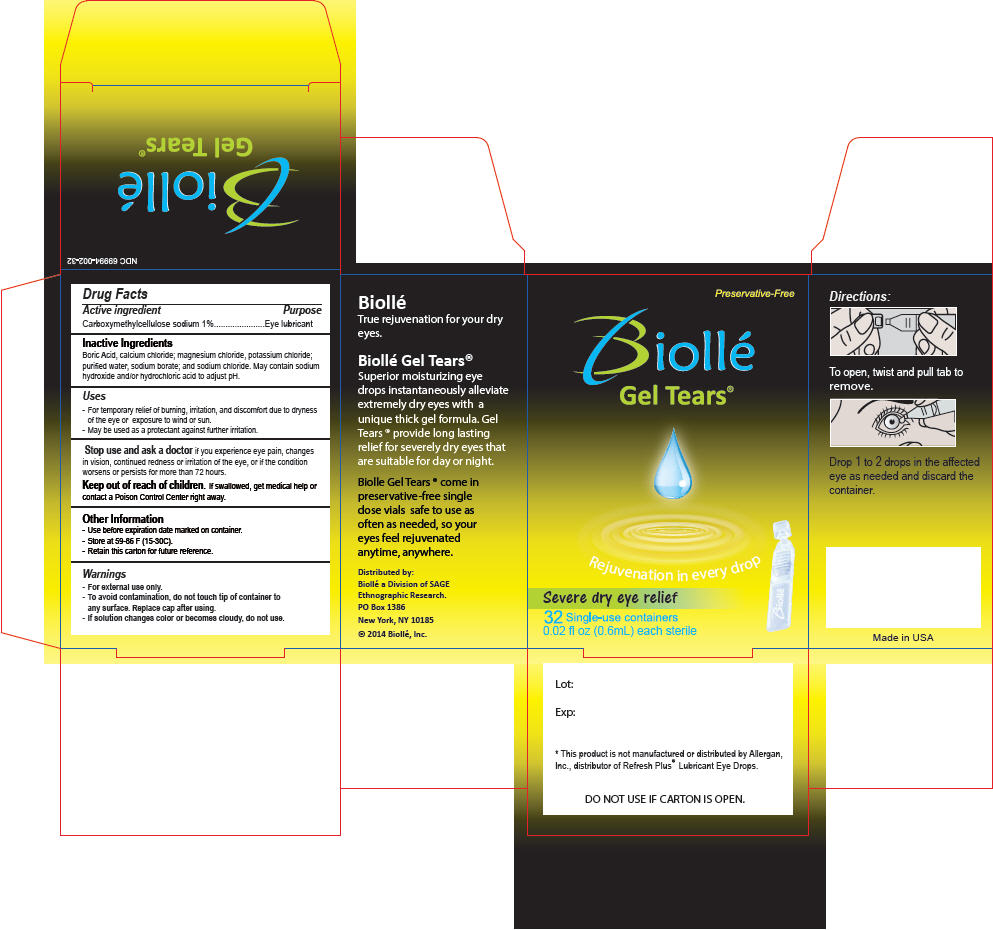 DRUG LABEL: Biolle  Gel Tears
NDC: 69994-002 | Form: SOLUTION/ DROPS
Manufacturer: SAGE Ethnographic Research, dba Biollé
Category: otc | Type: HUMAN OTC DRUG LABEL
Date: 20160413

ACTIVE INGREDIENTS: Carboxymethylcellulose Sodium, Unspecified Form 10 mg/1 mL
INACTIVE INGREDIENTS: Calcium Chloride; Magnesium Chloride; Potassium Chloride; Water; Sodium Chloride; Sodium Lactate; Hydrochloric Acid; Sodium Hydroxide

Biollé Gel Tears®

Drug Facts

Active ingredient

Carboxymethylcellulose sodium 1%

Purpose

Eye lubricant

Inactive Ingredients

Boric Acid, calcium chloride; magnesium chloride, potassium chloride; purified water, sodium borate; and sodium chloride. May contain sodium hydroxide and/or hydrochloric acid to adjust pH.

Uses

- For temporary relief of burning, irritation, and discomfort due to dryness of the eye or exposure to wind or sun.
- May be used as a protectant against further irritation.

Stop use and ask a doctor if you experience eye pain, changes in vision, continued redness or irritation of the eye, or if the condition worsens or persists for more than 72 hours.

Keep out of reach of children. If swallowed, get medical help or contact a Poison Control Center right away.

Other Information

- Use before expiration date marked on container.
- Store at 59-86 F (15-30C).
- Retain this carton for future reference.

Warnings

- For external use only.
- To avoid contamination, do not touch tip of container to any surface. Replace cap after using.
- If solution changes color or becomes cloudy, do not use.

Directions

To open, twist and pull tab to remove.

Drop 1 to 2 drops in the affected eye as needed and discard the container.

Distributed by:
Biollé Inc.
PO Box 1386
New York, NY 10185

PRINCIPAL DISPLAY PANEL - 32 Vial Carton

Preservative-Free

Biollé
Gel Tears®

Rejuvenation in every drop

Severe dry eye relief

32 Single-use containers
0.02 fl oz (0.6mL) each sterile